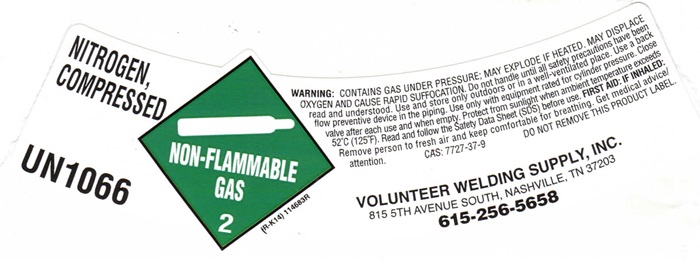 DRUG LABEL: NITROGEN
NDC: 53511-004 | Form: GAS
Manufacturer: Volunteer Welding Supply Inc
Category: prescription | Type: HUMAN PRESCRIPTION DRUG LABEL
Date: 20251126

ACTIVE INGREDIENTS: NITROGEN 99 L/100 L

Nitrogen

NITROGEN COMPRESSED LABEL

NITROGEN, COMPRESSED UN1066 NON-FLAMMABLE GAS 2 (R-K14) 114683R

WARNING: CONTAINS GAS UNDER PRESSURE; MAY EXPLODE IF HEATED. MAY DISPLACE OXYGEN AND CAUE RAPID SUFFOCATION. Do not handle until all safety precautions have been red and understood. Use and store only outdoors or in a well-ventilated place. Use a back flow preventive device in the piping. Use only with equipment rated for cylinder pressure. Close valve after each use and when empty. Protect from sunlight when ambient temperature exceeds 52°C (125°F0. Read and follow the Safety Data Sheet (SDS) before use. FIRST AIDE: IF INHALED: Remove person to fresh air and keep comfortable for breathing. Get medical advice/attention. CAS: 7727-37-9 DO ON REMOVE THIS PRODUCT LABEL.

VOLUNTEER WELDING SUPPLY, INC.

815 5TH AVENUE SOUTH, NASHVILLE, TN 37203

615-256-5658